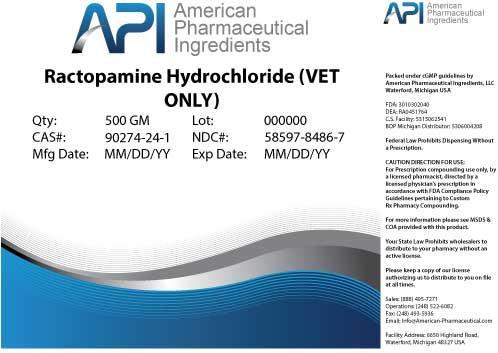 DRUG LABEL: Ractopamine Hydrochloride
NDC: 58597-8486 | Form: POWDER
Manufacturer: AMERICAN PHARMACEUTICAL INGREDIENTS LLC
Category: other | Type: BULK INGREDIENT
Date: 20140429

ACTIVE INGREDIENTS: Ractopamine Hydrochloride 1 g/1 g

Ractopamine Hydrochloride